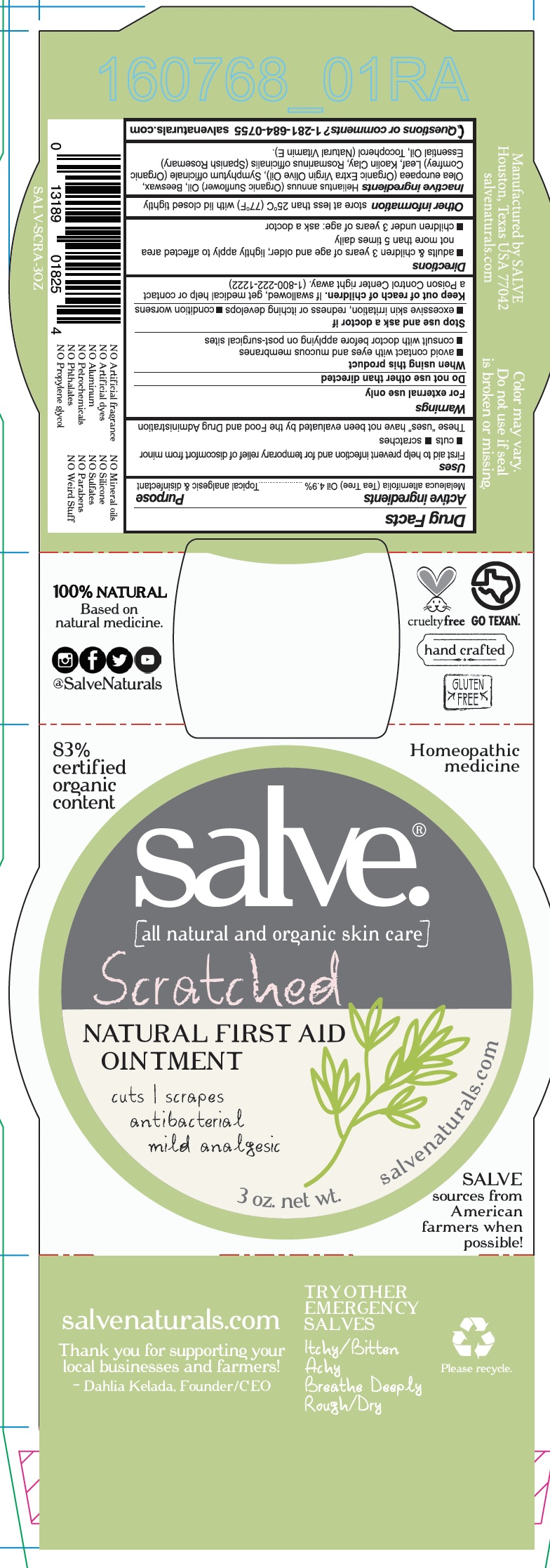 DRUG LABEL: Scratched
NDC: 71157-0021 | Form: OIL
Manufacturer: Kelada Creative Group
Category: homeopathic | Type: HUMAN OTC DRUG LABEL
Date: 20171016

ACTIVE INGREDIENTS: TEA TREE OIL 1089 g/90 mL
INACTIVE INGREDIENTS: SUNFLOWER OIL; WHITE WAX; ROSEMARY OIL; .ALPHA.-TOCOPHEROL; OLIVE OIL; COMFREY LEAF; KAOLIN

Scratched

ACTIVE INGREDIENT

Tea Tree Oil 4.9%

PURPOSE

First aid to help prevent infection and for temporary relief of discomfort from minor cuts and scratches

WARNINGS

For external use only

Do not use other than as directed

When using this product

- avoid contact with eyes and mucous membranes
- consult with doctor before applying on post-surgical sites

INDICATIONS AND USAGE

First aid to help prevent infection and for temporary relief of discomfort from minor cuts and scratches

DOSAGE AND ADMINISTRATION

Adults and children 3 years of age and older; lightly apply to affected area not more than 5 times daily

Children under 3 years of age; ask a doctor

Keep out of reach of children. If swallowed, get medical help or contact a Poison Control Center right away.

INACTIVE INGREDIENT

Organic sunflower oil, Beeswax, Organic extra virgin olive oil, Organic comfrey leaf, Kaolin clay, Spanish Rosemary essential oil, Natural Vitamin E